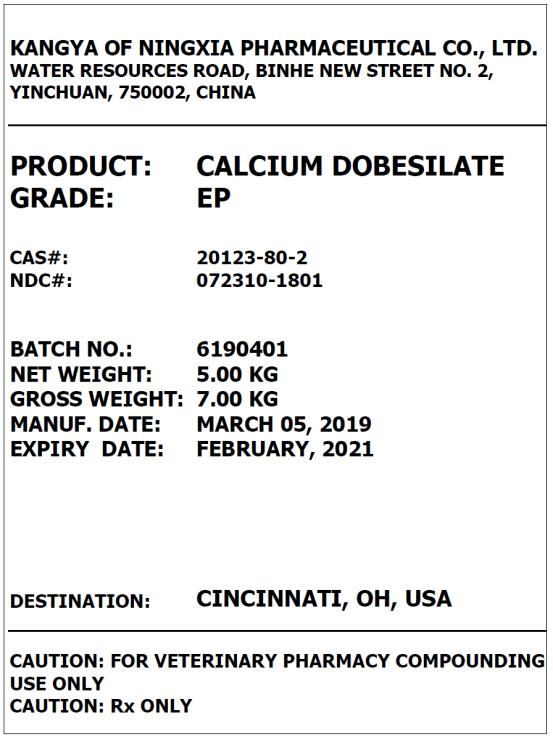 DRUG LABEL: Calcium Dobesilate
NDC: 72310-1801 | Form: POWDER
Manufacturer: Kangya of Ningxia Pharmaceutical Co., Ltd.
Category: other | Type: BULK INGREDIENT
Date: 20190625

ACTIVE INGREDIENTS: CALCIUM DOBESILATE 1 kg/1 kg

CALCIUM DOBESILATE

PRINCIPAL DISPLAY PANEL – BULK PRODUCT

KANGYA OF NINGXIA PHARMACEUTICAL CO., LTD.

WATER RESOURCES ROAD BINHE NEW STREET NO. 2, YINCHUAN, 750002, CHINA

PRODUCT: CALCIUM DOBESILATE
GRADE: EP

CAS#: 20123-80-2
NDC#: 72310-1801

CAUTION: FOR PHARMACY COMPOUNDING USE ONLY
CAUTION: Rx ONLY